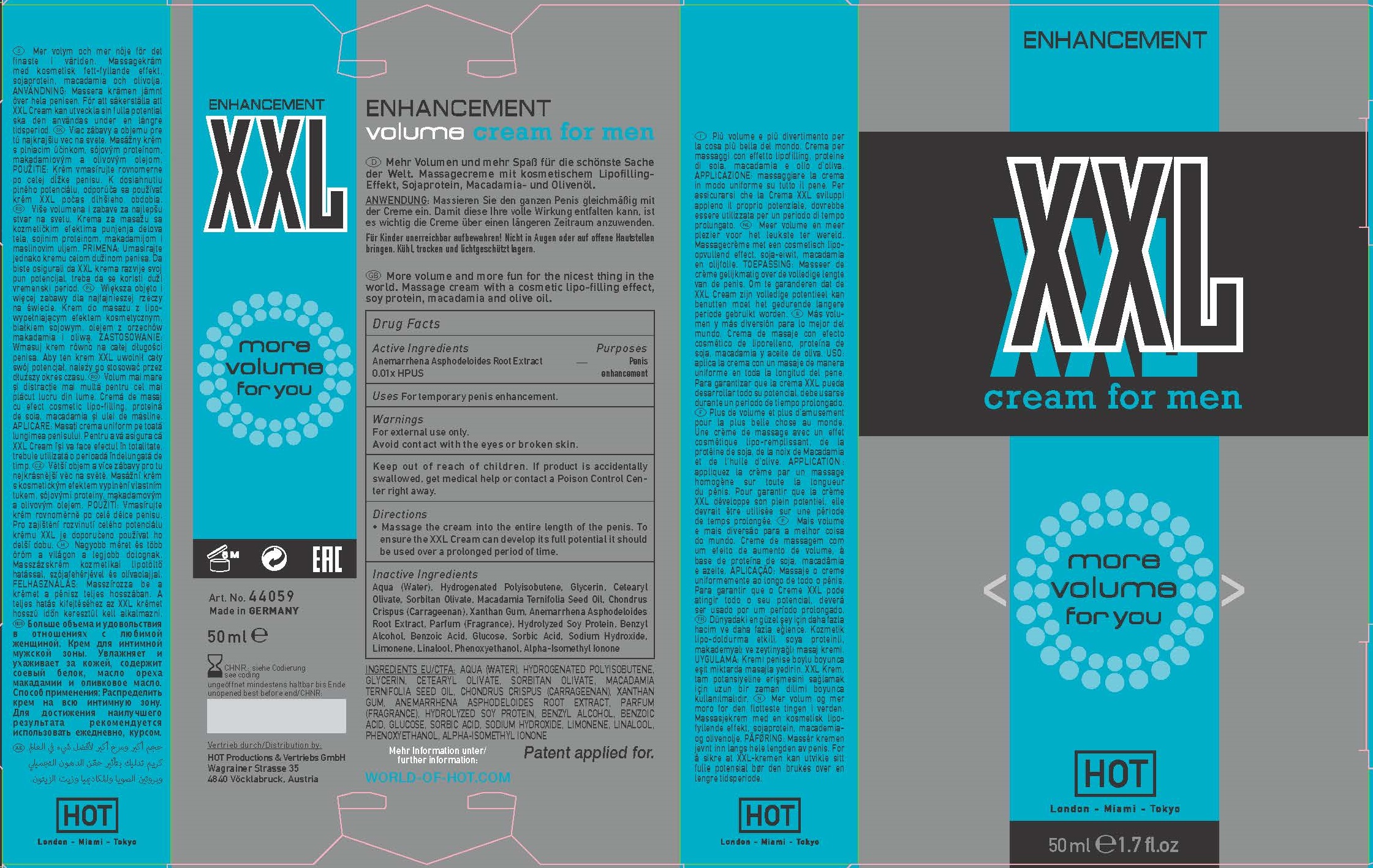 DRUG LABEL: XXL FOR MEN
NDC: 71326-303 | Form: CREAM
Manufacturer: HOT PRODUCTIONS AND VERTRIEBS GMBH
Category: homeopathic | Type: HUMAN OTC DRUG LABEL
Date: 20231005

ACTIVE INGREDIENTS: ANEMARRHENA ASPHODELOIDES ROOT 0.1 g/100 mL
INACTIVE INGREDIENTS: WATER; HYDROGENATED POLYBUTENE (1300 MW); GLYCERIN; CETEARYL OLIVATE; SORBITAN OLIVATE; MACADAMIA OIL; BENZYL ALCOHOL; CHONDRUS CRISPUS CARRAGEENAN; XANTHAN GUM; HYDROLYZED SOY PROTEIN (ENZYMATIC; 2000 MW); BENZOIC ACID; DEXTROSE, UNSPECIFIED FORM; SORBIC ACID; SODIUM HYDROXIDE; LIMONENE, (+)-; LINALOOL, (+)-; PHENOXYETHANOL; ISOMETHYL-.ALPHA.-IONONE

HOT PRODUCTS - XXL Cream for Men (71326-303)

ACTIVE INGREDIENTS

Anemarrhena Asphodeloides 0.01x HPUS

PURPOSE

Penis enhancement

USE

AFor temporary penis enhancement

WARNINGS

For external use only.
Avoid contact with the eyes or broken skin.

Keep out of reach of children. If product is accidentally swallowed, get medical help or contact a Poison Control Center right away.

DIRECTIONS

- • Massage the cream into the entire length of the penis. To ensure the XXL Cream can develop its full potential it should be used over a prolonged period of time

INACTIVE INGREDIENTS

Aqua (Water), Hydrogenated Polyisobutene, Glycerin, Cetearyl Olivate, Sorbitan Olivate, Macadamia Ternifolia Seed Oil, Chondrus Crispus (Carrageenan), Xanthan Gum, Anemarrhena Asphodeloides Root Extract, Parfum (Fragrance), Hydrolyzed Soy Protein, Benzyl Alcohol, Benzoic Acid, Glucose, Sorbic Acid, Sodium Hydroxide, Limonene, Linalool, Phenoxyethanol, Alpha-Isomethyl Ionone